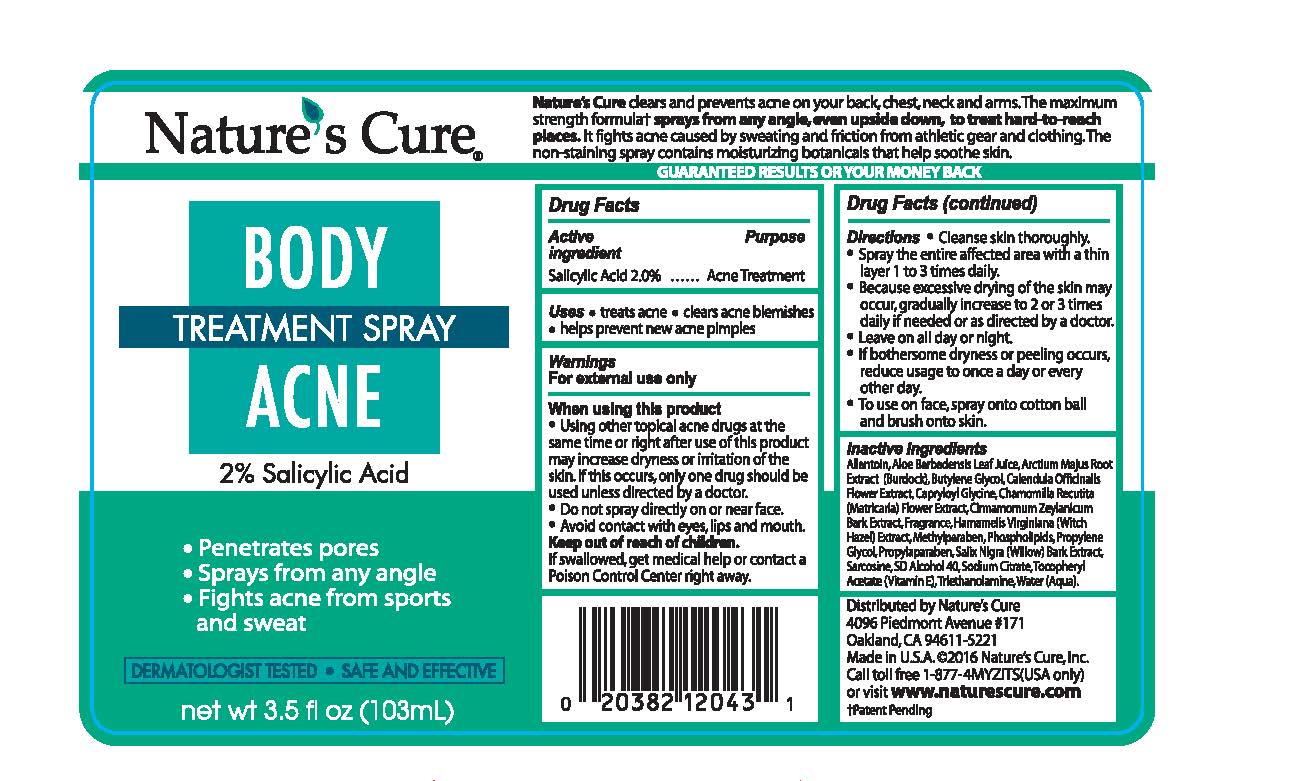 DRUG LABEL: Natures Cure Body Acne Treatment
NDC: 21839-680 | Form: SPRAY
Manufacturer: Gordon Laboratories, Inc.
Category: otc | Type: HUMAN OTC DRUG LABEL
Date: 20191230

ACTIVE INGREDIENTS: SALICYLIC ACID 20 mg/1 mL
INACTIVE INGREDIENTS: PROPYLENE GLYCOL; METHYLPARABEN; HAMAMELIS VIRGINIANA TOP; CINNAMON BARK OIL; CAPRYLOYL GLYCINE; CALENDULA OFFICINALIS FLOWER; WATER; LECITHIN, SOYBEAN; ARCTIUM LAPPA ROOT; SALIX NIGRA BARK; PROPYLPARABEN; SODIUM CITRATE; TROLAMINE; ALPHA-TOCOPHEROL ACETATE; ALCOHOL; SARCOSINE; CHAMOMILE; ALOE VERA LEAF; ALLANTOIN

Natures Cure Body Acne Treatment Spray 2% Salicylic Acid

Drug Facts

Active ingredient

Salicylic Acid 2.0%

Purpose

Acne Treatment

Uses

* treats acne * clears acne blemishes * helps prevent new acne pimples

Warnings

For external use only

Warnings

For external use only

When using this product

* Using other topical acne drugs at the same time or right after use of this product may increase dryness or irritation of the skin. If this occurs, only one drug should be used unless directed by a doctor.

* Do not spray directly on or near face.

* Avoid contact with eyes, lips and mouth.

Keep out of reach of children.

If swallowed, get medical help or contact a Poison Control Center right away.

DOSAGE AND ADMINISTRATION

Directions * Cleanse skin thoroughly.

*Spray the entire affected area with a thin layer 1 to 3 times daily.

*Because excessive drying of the skin may occur, gradually increase to 2 or 3 times daily if needed or as directed by a doctor.

* Leave on all day or night.

* If bothersome dryness or peeling occurs, reduce usage to once a day or every other day.

* To use on face, spray onto cotton ball and brush onto skin.

DESCRIPTION

Nature's Cure clears and prevents acne on your back, chest, neck and arms. The maximum strength formula sprays from any angle, even upside down, to treat hard-to-reach places. It fights acne caused by sweating and friction from athletic gear and clothing. The non-staining spray contains moisturizing botanicals that help soothe skin.

INACTIVE INGREDIENT

Allantoin, Aloe Barbadensis Leaf Juice, Arctium Majus Root Extract (Burdock), Calendula Officinalis Flower Extract, Capryloyl Glycine, Chamomilla Recutita (Matricaria) Flower Extract, Cinnamomum Zeylanicum Bark Water Extract, Fragrance, Hamamelis Virginiana (Witch Hazel) Extract, Methylparaben, Phospholipids, Propylene Glycol, Propylparaben, Salix Nigra (Willow) Bark Extract, Sarcosine, SD Alcohol 40, Sodium Citrate, Tocopheryl Acetate (Vitamin E), Triethanolamine, Water (Aqua).

QUESTIONS

Call toll free 1-877-4MYZITS(USA only)

or visit www.naturescure.com